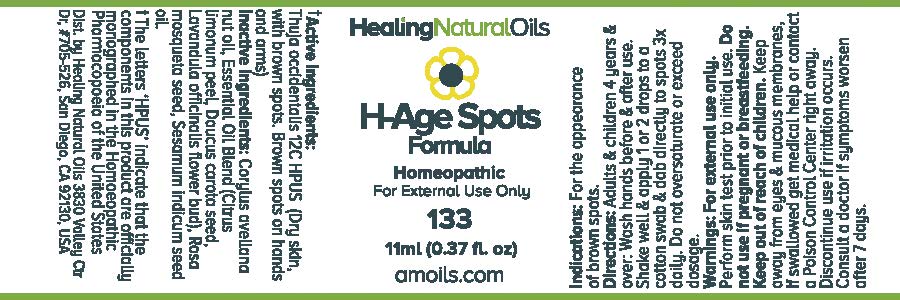 DRUG LABEL: H-Age Spots Formula
NDC: 61077-133 | Form: OIL
Manufacturer: Healing Natural Oils LLC
Category: homeopathic | Type: HUMAN OTC DRUG LABEL
Date: 20171227

ACTIVE INGREDIENTS: THUJA OCCIDENTALIS LEAFY TWIG 12 [hp_C]/11 mL
INACTIVE INGREDIENTS: EUROPEAN HAZELNUT OIL 12 [hp_C]/11 mL; LEMON JUICE; DAUCUS CAROTA SUBSP. SATIVUS SEED; LAVANDULA ANGUSTIFOLIA FLOWERING TOP; ROSA RUBIGINOSA SEED OIL; SESAME OIL

Active Ingredients:

Thuja occidentalis 12C HPUS

Purpose

Thuja occidentalis 12C HPUS (Dry skin, with brown spots. Brown spots on hands and arms)

The letters ‘HPUS’ indicate that the components in this product are officially monographed in the Homoeopathic Pharmacopoeia of the United States

Inactive Ingredients:

Corylus avellana nut oil, Essential Oil Blend (Citrus limonum peel, Daucus carota seed, Lavandula officinalis flower bud), Rosa mosqueta
seed oil, sesamum indicum seed oil.

Indications:

For the appearance of brown spots.

Directions:

Adults and Children 4 years and over: Wash hands before and after use. Shake well and apply 1 or 2 drops to a cotton swab and dab directly to spots 3x daily. Do not oversaturate or exceed dosage.

Warnings:

For external use only.
Perform skin test prior to initial use.

Do not use if pregnant or breastfeeding.

Keep out of reach of children.

OTHER SAFETY INFORMATION

Keep away from eyes and mucous membranes. If swallowed get medical help or contact a Poison Control
Center right away.

Discontinue use if irritation occurs.

ASK DOCTOR

Consult a doctor if symptoms worsen after 7 days.

DESCRIPTION

Dist. by Healing Natural Oils 3830 Valley Ctr Dr, #705-526, San Diego, CA 92130, USA

PACKAGE LABEL

Healing Natural Oils

H-Age Spots
Formula

Homeopathic

For External Use Only

133

11ml (0.37 fl. oz)

amolis.com